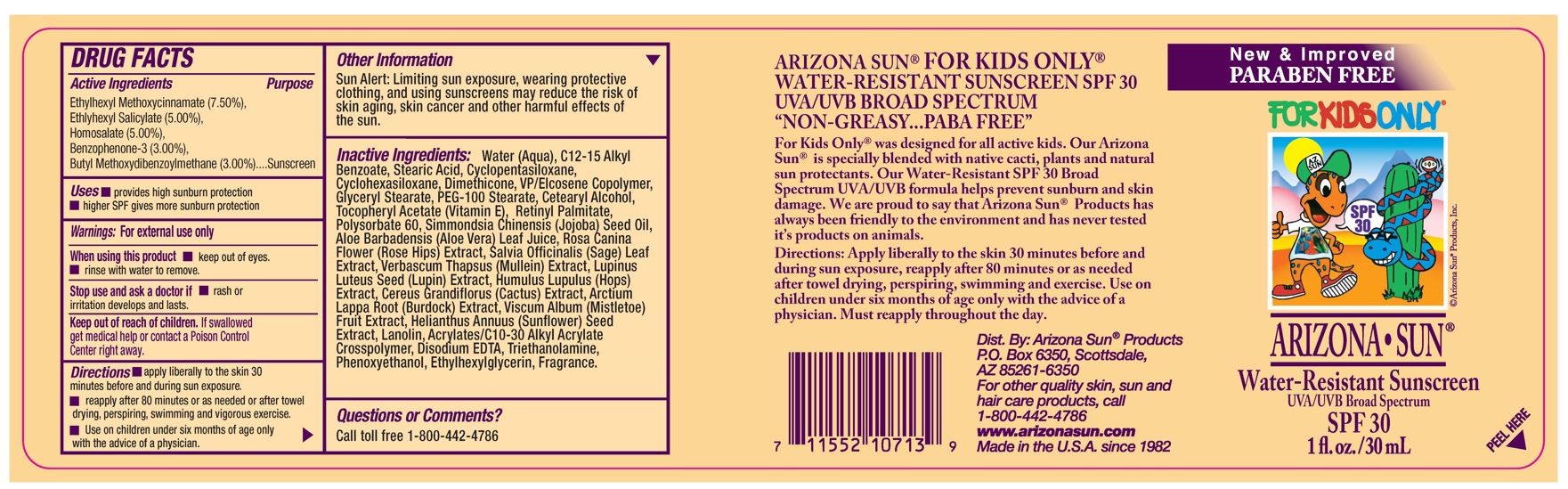 DRUG LABEL: Arizona Sun Sunscreen Kids Water Resistant SPF 30
NDC: 61973-106 | Form: LOTION
Manufacturer: Arizona Sun Products
Category: otc | Type: HUMAN OTC DRUG LABEL
Date: 20240215

ACTIVE INGREDIENTS: OXYBENZONE 30 mg/1 g; OCTINOXATE 75 mg/1 g; AVOBENZONE 30 mg/1 g; OCTISALATE 50 mg/1 g; HOMOSALATE 50 mg/1 g
INACTIVE INGREDIENTS: ALKYL (C12-15) BENZOATE; CYCLOMETHICONE 7; CYCLOMETHICONE 6; .ALPHA.-TOCOPHEROL ACETATE; ROSA CANINA FLOWER; MULLEIN LEAF; GLYCERYL STEARATE SE; VINYLPYRROLIDONE/EICOSENE COPOLYMER; VISCUM ALBUM FRUIT; DIMETHICONE; LUPINUS LUTEUS SEED; HOPS; WATER; LANOLIN; ACRYLATES/C10-30 ALKYL ACRYLATE CROSSPOLYMER (60000 MPA.S); TROLAMINE; PHENOXYETHANOL; SELENICEREUS GRANDIFLORUS FLOWER; SUNFLOWER SEED; DISODIUM EDTA-COPPER; PEG-100 STEARATE; VITAMIN A PALMITATE; POLYSORBATE 60; SAGE; ETHYLHEXYLGLYCERIN; ALOE VERA LEAF; STEARYL ALCOHOL; SIMMONDSIA CHINENSIS SEED; ARCTIUM LAPPA ROOT

1 oz Kids Water Resistant SPF 30

Active Ingredients

Ethylhexyl Methoxycinnamate (7.50%), Ethylhexyl Salicylate (5.00%), Homosalate (5.00%), Benzophenone-3 (3.00%), Butyl Methoxydibenzoylmethane (3.00%)

Purpose

Sunscreen

Uses

Provides high sunburn protection. Higher SPF gives more sunburn protection.

Warnings

For external use only.

When using this product

keep out of eyes. Rinse with water to remove.

Stop and ask a doctor if

rash or irritation develops and lasts.

Keep out of the reach of children.

If swallowed get medical help or contact a poison control center right away.

Directions

Apply liberally and evenly to the skin 30 minutes before and during sun exposure. Reapply as needed or after towel drying, perspiring, swimming, and vigorous activities. Use on children under six months of age only wih the advise of a physician.

Other Information

Sun Alert: Limiting sun exposure, wearing protective clothing, and using suscreen may reduce the risk of skin aging, skin cancer and other harmful effects of the sun.

Inactive Ingredients

Water, C12-15 Alkyl Benzoate, Stearic Acid, Cyclopentasiloxane, Cyclohexasiloxane, Dimethicone, VP/ Eicosene Copolymer, Glyceryl Stearate, PEG-100 Stearate, Cetearyl Alcohol, Tocopheryl Acetate (Vitamin E), Retinyl Palmitate, Polysorbate 60, Simmondsia Chinensis (Jojoba) Seed Oil, Aloe Barbadensis (Aloe Vera) Leaf Juice, Rosa Canina Flower (Rose Hips) Extract, Salvia Officinalis (Sage) Leaf Extract, Verbascum Thapsus (Mullein) Extract, Lupinus Luteus Seed (Lupin) Extract, Humulus Lupulus (Hops) Extract, Cereus Grandiflorus (Cactus) Extract, Arctium Lappa Root (Burdock) Extract, Visicum Album (Mistletoe) Fruit Extract, Helianthus Annuus (Sunflower) Seed Extract, Lanolin, Acrylates/ C10-30 Alkyl Acrylate Crosspolymer, Disodium EDTA, Triethanolamine, Phenoxyethanol, Ethylhexylglycerin, Fragrance

Questions or Comments

Call toll free 1-800-442-4786